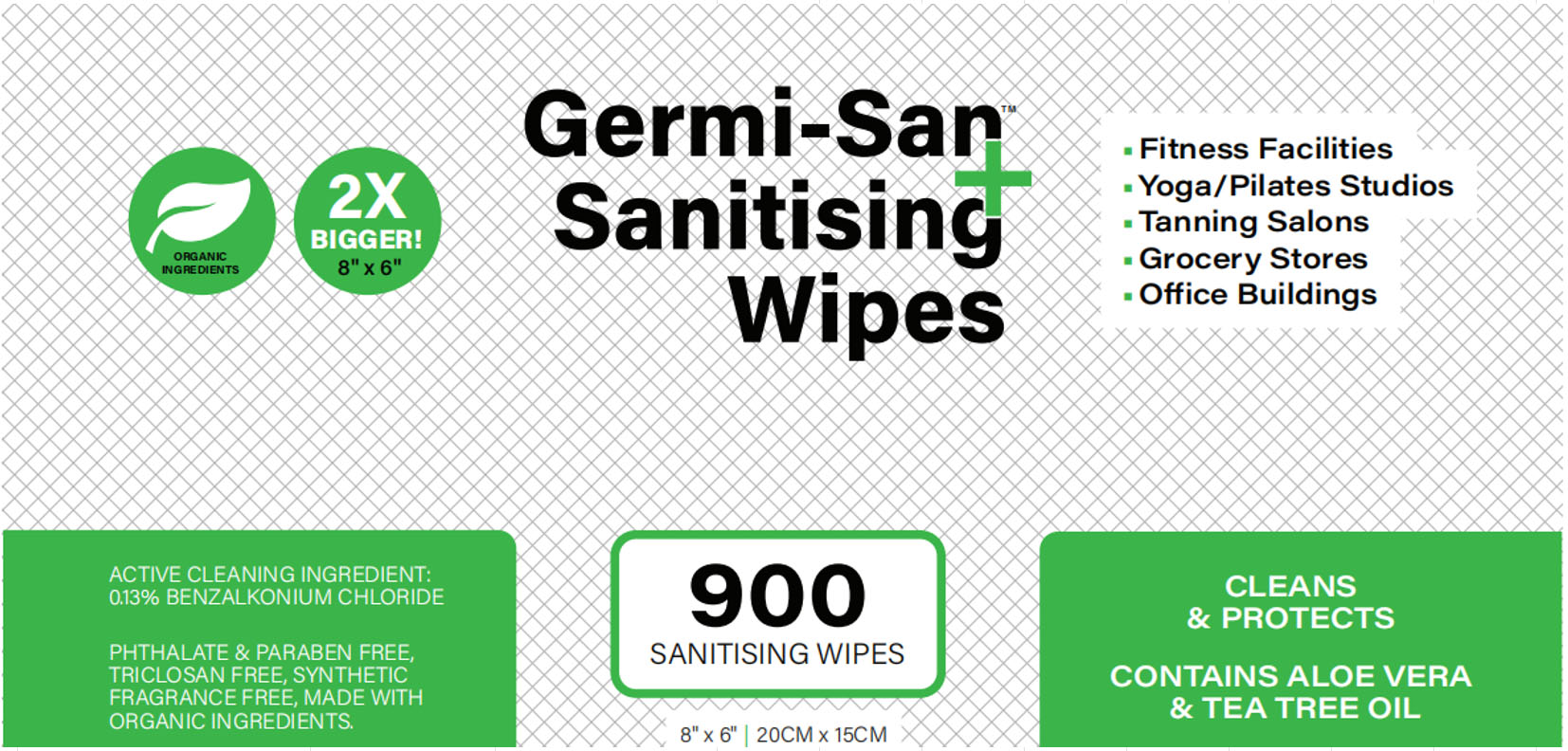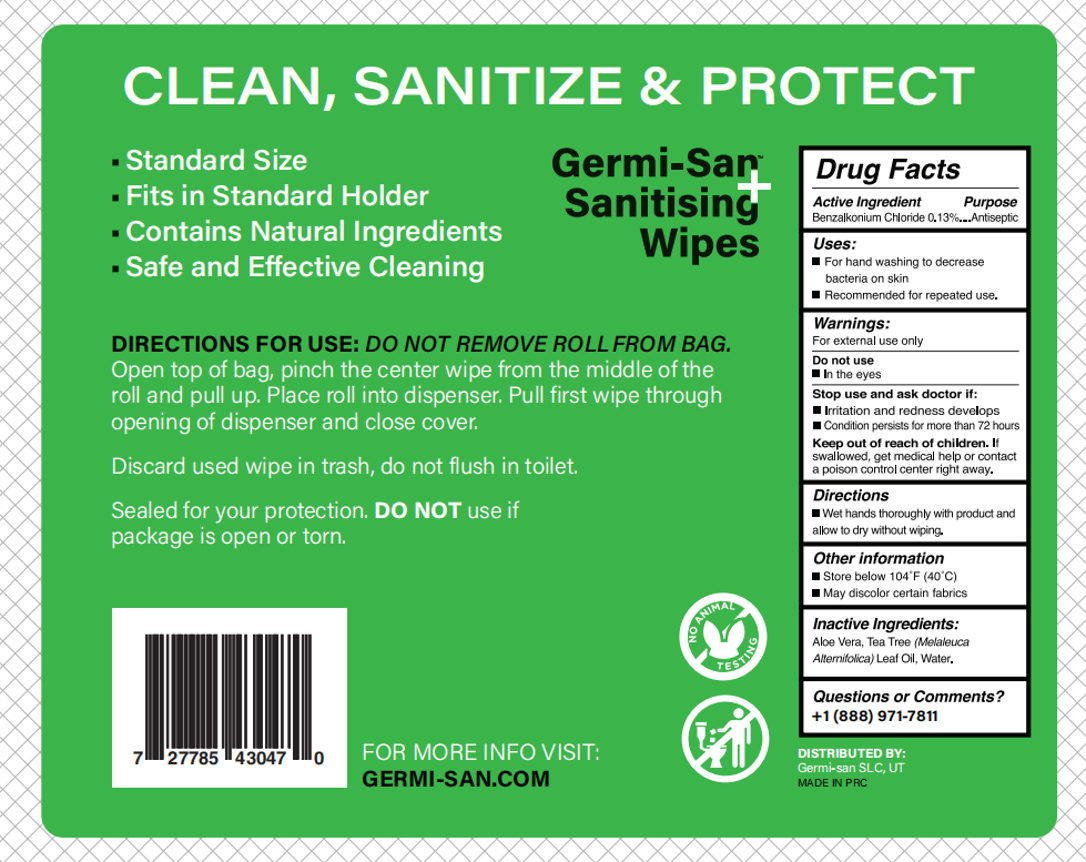 DRUG LABEL: ANTISEPTIC SANITIZING WIPES
NDC: 83666-001 | Form: CLOTH
Manufacturer: ZHEJIANG WIPEX NEW MATERIAL TECHNOLOGY CO.,LTD
Category: otc | Type: HUMAN OTC DRUG LABEL
Date: 20231219

ACTIVE INGREDIENTS: BENZALKONIUM CHLORIDE 0.013 g/1 g
INACTIVE INGREDIENTS: SODIUM CITRATE; MENTHOL; POLYSORBATE 20; BENZOIC ACID; POTASSIUM SORBATE; MELALEUCA ALTERNIFOLIA (TEA TREE) LEAF OIL; GLYCERIN; PHENOXYETHANOL; WATER; ALOE VERA LEAF; DISODIUM COCOAMPHODIACETATE

ANTISEPTIC SANITIZING WIPES

ANTISEPTIC SANITIZING WIPES

ACTIVE INGREDIENT

Benzalkonium Chloride 0.13%

PURPOSE

For hand washing to decrease bacteria on skin

Recommended for repeated use.

INDICATIONS AND USAGE

For hand washing to decrease bacteria on skin

Recommended for repeated use.

WARNINGS

For external use only

DO NOT USE

In the eyes

WHEN USING

Wet hands thoroughly with product andallaw to dry without wiping.

STOP USE

lrritation and redness develops
Condition persists for more than 72 hours

Keep out of reach of children. If
swallowed, get medical help or contacta poison control center right away.

DOSAGE AND ADMINISTRATION

Wet hands thoroughly with product andallow to dry without wiping.

STORAGE AND HANDLING

Store below 104F(40°C)
May discolor certain fabrics

INACTIVE INGREDIENT

water
Glycerin
Disodium Cocoamphodiacetate
Phenoxyethanol
Benzoic Acid
Polysorbate 20
Potassium Sorbate
Aloe barbadensia Leaf juice
Benzalkonium Chloride
Melaleuca Alternifolia (Tea Tree) Leaf Oil
Menthol
Sodium Citrate